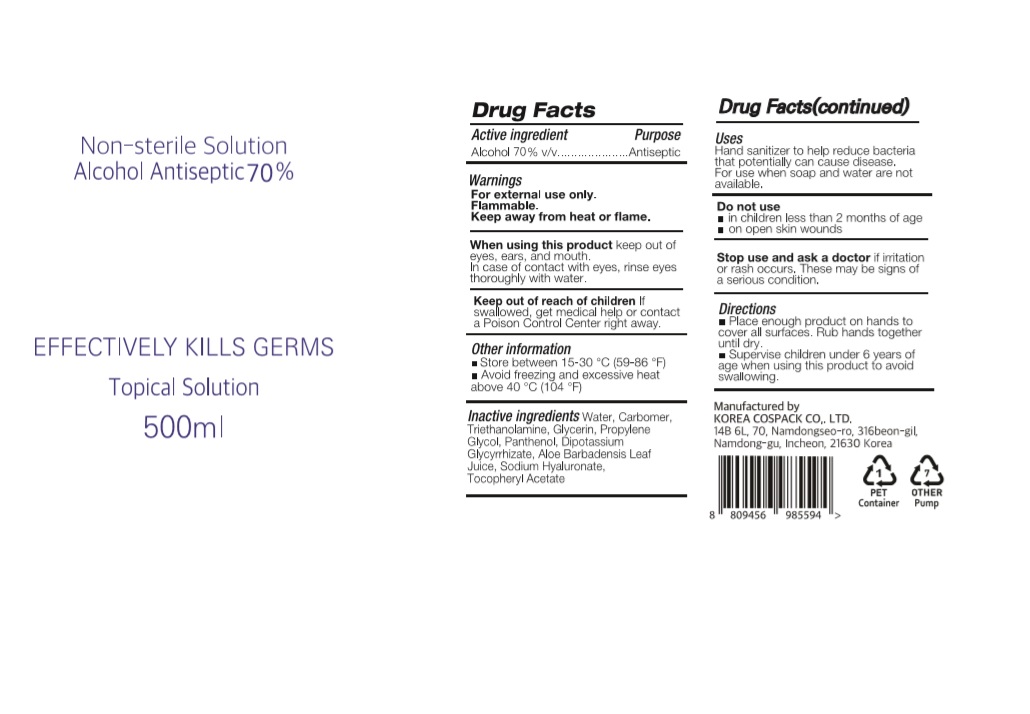 DRUG LABEL: CLEAN TO CLEAN HAND SANITIZER Gel PLUS
NDC: 74064-5071 | Form: GEL
Manufacturer: KOREA COSPACK CO.,LTD.
Category: otc | Type: HUMAN OTC DRUG LABEL
Date: 20200526

ACTIVE INGREDIENTS: ALCOHOL 350 mL/500 mL
INACTIVE INGREDIENTS: GLYCERIN; CARBOMER HOMOPOLYMER, UNSPECIFIED TYPE; WATER; PROPYLENE GLYCOL; PANTHENOL; GLYCYRRHIZINATE DIPOTASSIUM; ALOE VERA LEAF; .ALPHA.-TOCOPHEROL ACETATE; HYALURONATE SODIUM; TROLAMINE

CLEAN TO CLEAN HAND SANITIZER GEL PLUS 500ml BOTTLE+PUMP
74064-5071-1